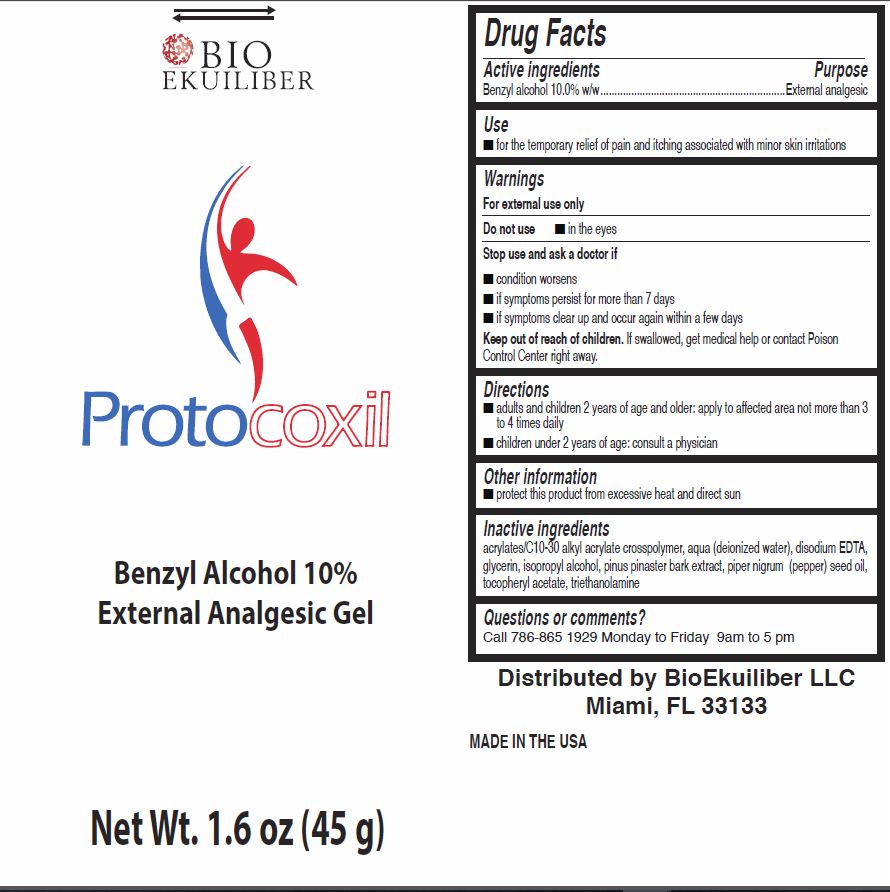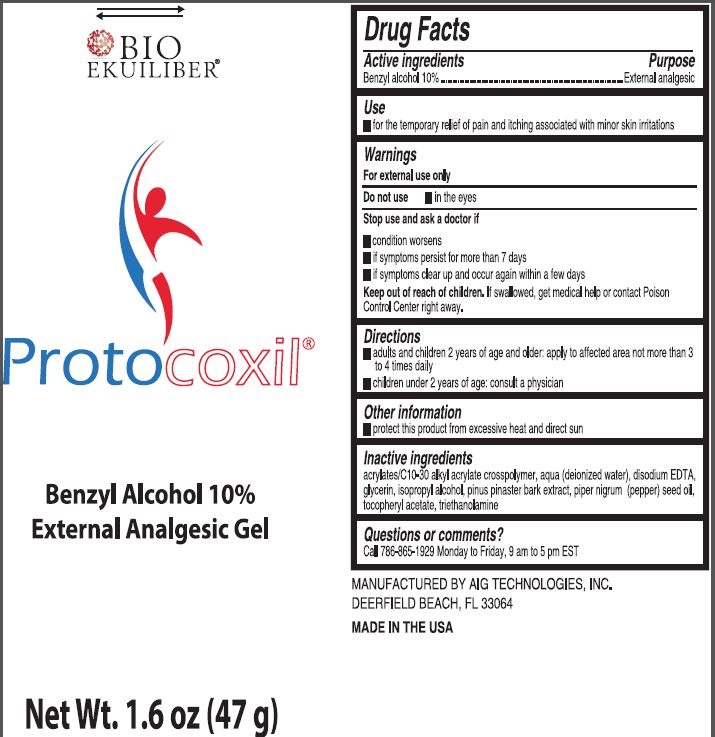 DRUG LABEL: Protocoxil
NDC: 71416-001 | Form: GEL
Manufacturer: Bio Ekuiliber LLC
Category: otc | Type: HUMAN OTC DRUG LABEL
Date: 20201127

ACTIVE INGREDIENTS: BENZYL ALCOHOL 100 mg/1 g
INACTIVE INGREDIENTS: CARBOMER INTERPOLYMER TYPE A (ALLYL SUCROSE CROSSLINKED); WATER; EDETATE DISODIUM ANHYDROUS; GLYCERIN; ISOPROPYL ALCOHOL; MARITIME PINE; WHITE PEPPER OIL; .ALPHA.-TOCOPHEROL ACETATE; TROLAMINE

Protocoxil

Active ingredients

Benzyl alcohol 10%

Purpose

External analgesic

Use

- for the temporary relief of pain and itching associated with minor skin irritations

Warnings

For external use only

Do not use

- in the eyes

Stop use and ask a doctor if

- condition worsens
- if symptoms persist for more than 7 days
- if symptoms clear up and occur again within a few days

Keep out of reach of children.

If swallowed, get medical help or contact Poison Control Center right away.

Directions

- adults and children 2 years of age and older: apply to affected area not more than 3 to 4 times daily
- children under 2 years of age: consult a physician

Other information

- protect this product from excessive heat and direct sun

Inactive ingredients

acrylates/C10-30 alkyl acrylate crosspolymer, aqua (deionized water), disodium EDTA, glycerin, isopropyl alcohol, pinus pinaster bark extract, piper nigrum (pepper) seed oil, tocopheryl acetate, triethanolamine

Questions or comments?

Call 786-230-6366 Monday to Friday, 9 am to 5 pm EST